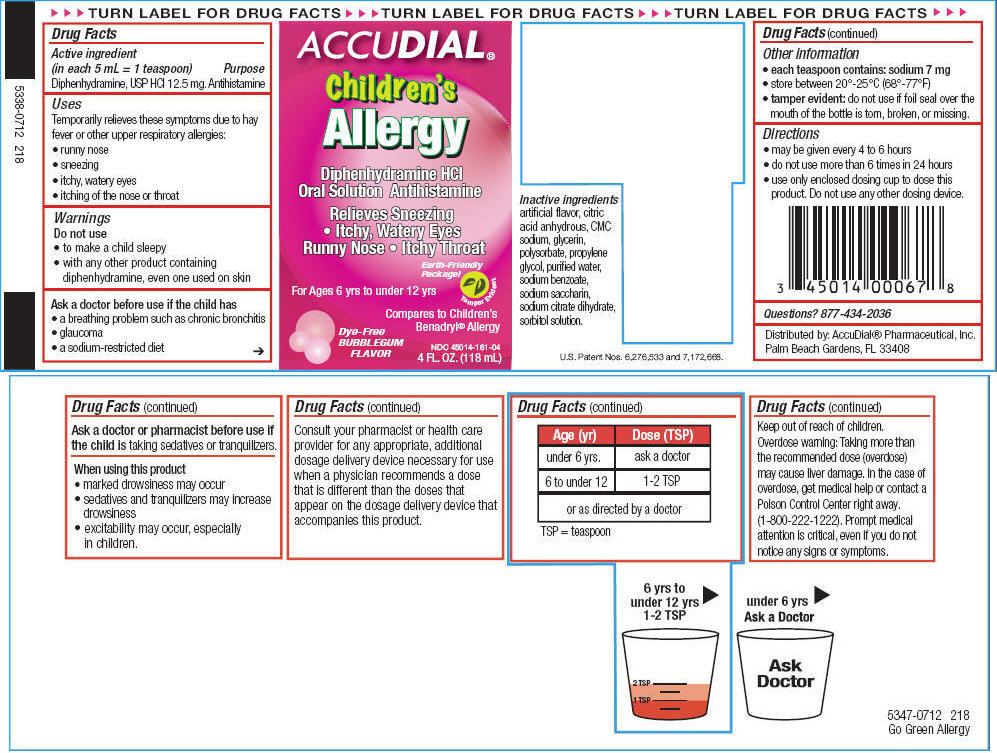 DRUG LABEL: Allergy
NDC: 45014-161 | Form: LIQUID
Manufacturer: Accudial Pharmaceutical, Inc.
Category: otc | Type: HUMAN OTC DRUG LABEL
Date: 20130206

ACTIVE INGREDIENTS: Diphenhydramine Hydrochloride 12.5 mg/5 mL
INACTIVE INGREDIENTS: Anhydrous Citric Acid; Sodium; Glycerin; Polysorbate 20; Propylene Glycol; Water; Sodium Benzoate; Saccharin Sodium; Trisodium Citrate Dihydrate; Sorbitol

Allergy

Drug Facts

Active ingredient (in each 5 mL = 1 teaspoon)

Diphenhydramine, USP HCl 12.5 mg.

Purpose

Antihistamine

Uses

Temporarily relieves these symptoms due to hay fever or other upper respiratory allergies:

- runny nose
- sneezing
- itchy, watery eyes
- itching of the nose or throat

Warnings

Do not use

- to make a child sleepy
- with any other product containing diphenhydramine, even one used on skin

Ask a doctor before use if the child has

- a breathing problem such as chronic bronchitis
- glaucoma
- a sodium-restricted diet

Ask a doctor or pharmacist before use if the child is taking sedatives or tranquilizers.

When using this product

- marked drowsiness may occur
- sedatives and tranquilizers may increase drowsiness
- excitability may occur, especially in children.

ASK DOCTOR/PHARMACIST

Consult your pharmacist or health care provider for any appropriate, additional dosage delivery device necessary for use when a physician recommends a dose that is different than the doses that appear on the dosage delivery device that accompanies this product.

Age (yr) | Dose (TSP)
under 6 yrs. | ask a doctor
6 to under 12 | 1-2 TSP
or as directed by a doctor
TSP = teaspoon

Keep out of reach of children.

Overdose warning

Taking more than the recommended dose (overdose) may cause liver damage. In the case of overdose, get medical help or contact a Poison Control Center right away. (1-800-222-1222). Prompt medical attention is critical, even if you do not notice any signs or symptoms.

Other information

- each teaspoon contains: sodium 7 mg
- store between 20°-25°C (68°-77°F)
- tamper evident: do not use if foil seal over the mouth of the bottle is torn, broken, or missing.

Directions

- may be given every 4 to 6 hours
- do not use more than 6 times in 24 hours
- use only enclosed dosing cup to dose this product. Do not use any other dosing device.

Questions?

877-434-2036

Inactive ingredients

artificial flavor, citric acid anhydrous, CMC sodium, glycerin, polysorbate, propylene glycol, purified water, sodium benzoate, sodium saccharin, sodium citrate dihydrate, sorbitol solution.

Distributed by: AccuDial® Pharmaceutical, Inc. Palm Beach Gardens, FL 33408

PRINCIPAL DISPLAY PANEL - 118 mL Bottle Label

ACCUDIAL®

Children's
Allergy

Diphenhydramine HCl
Oral Solution Antihistamine

Relieves Sneezing
• Itchy, Watery Eyes
Runny Nose • Itchy Throat

Earth-Friendly
Package!

For Ages 6 yrs to under 12 yrs

Tamper Evident

Compares to Children's
Benadryl® Allergy

Dye-Free
BUBBLEGUM
FLAVOR

NDC 45014-161-04
4 FL. OZ. (118 mL)